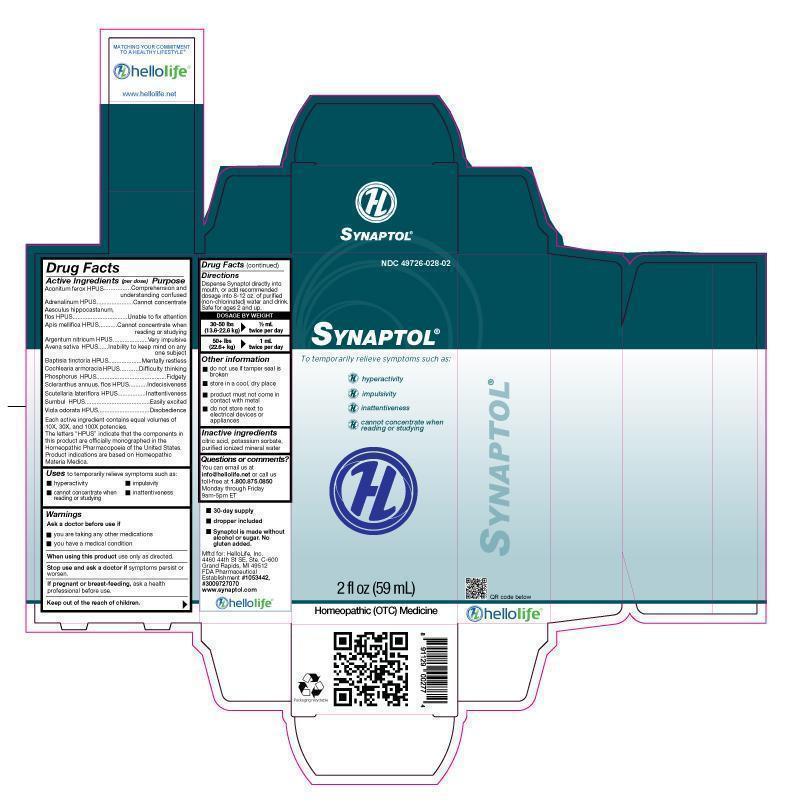 DRUG LABEL: Synaptol
NDC: 49726-028 | Form: LIQUID
Manufacturer: Hello Life, Inc.
Category: homeopathic | Type: HUMAN OTC DRUG LABEL
Date: 20181226

ACTIVE INGREDIENTS: ACONITUM FEROX ROOT 100 [hp_X]/59 mL; EPINEPHRINE 100 [hp_X]/59 mL; AESCULUS HIPPOCASTANUM FLOWER 100 [hp_X]/59 mL; APIS MELLIFERA 100 [hp_X]/59 mL; SILVER NITRATE 100 [hp_X]/59 mL; AVENA SATIVA FLOWERING TOP 100 [hp_X]/59 mL; BAPTISIA TINCTORIA ROOT 100 [hp_X]/59 mL; HORSERADISH 100 [hp_X]/59 mL; PHOSPHORUS 100 [hp_X]/59 mL; SCLERANTHUS ANNUUS FLOWERING TOP 100 [hp_X]/59 mL; SCUTELLARIA LATERIFLORA 100 [hp_X]/59 mL; FERULA SUMBUL ROOT 100 [hp_X]/59 mL; VIOLA ODORATA 100 [hp_X]/59 mL
INACTIVE INGREDIENTS: CITRIC ACID MONOHYDRATE; POTASSIUM SORBATE; WATER

Drug Facts

Active Ingredients (per dose)

Aconitum ferox HPUS

Adrenalinum HPUS

Aesculus hippocastanum flos HPUS

Apis mellifica HPUS

Argentum nitricum HPUS

Avena sativa HPUS

Baptisia tinctoria HPUS

Cochlearia armoracia HPUS

Phosphorus HPUS

Scleranthus annuus, flos HPUS

Scutellaria lateriflora HPUS

Sumbul HPUS

Viola odorata HPUS

Each active ingredient contains equal volumes of 10X, 30X, and 100X potencies. The letters "HPUS" indicate that the components in this product are officially monographed in the Homeopathic Pharmacopoeia of the United States. Product indications are based on Homeopathic Materia Medica.

Purpose

Aconitum ferox HPUS........................................Comprehension and understanding confused

Adrenalinum HPUS...................................Cannot concentrate

Aesculus hippocastanum flos HPUS......................Unable to fix attention

Apis mellifica HPUS...........................Cannot concentrate when reading or studying
Argentum nitricum HPUS.........................................Very impulsive
Avena sativa HPUS.............................................Inability to keep mind on any one subject
Baptisia tinctoria HPUS......................................Mentally resless
Cochlearia armoracia HPUS................................Difficulty thinking
Phosphorus HPUS.......................................................Fidgety
Scleranthus annuus, flos HPUS.............................Indecisiveness
Scutellaria lateriflora HPUS...................................Inattentiveness
Sumbul HPUS..............................................................Easily excited
Viola odorata HPUS.......................Disobedience

Uses

For temporary relief of symptoms such as:

- hyperactivity
- difficulty reading and writing
- cannot concentrate when reading or studying
- inattentivness

Warnings

Ask a doctor before use if

- you are taking any other medications
- you have a medical condition

When using this product, use only as directed.

Stop use and ask a doctor if symptoms persist or worsen.

PREGNANCY OR BREAST FEEDING

If pregnant or breast-feeding, ask a health professional before use.

Keep out of the reach of children.

Directions

Dispense Synaptol directly into mouth, or add recommended dosage into 8-12 oz. of purified (non-chlorinated) water and drink.

DOSAGE BY WEIGHT

30-50 LBS (13.6-22.6 kg) -> 1/2 mL twice per day

50+ lbs (22.6+ kg) -> 1 mL twice per day

Other information

- do not use if tamper seal is broken
- store in a cool, dry place
- product must not come in contact with metal
- do not store next to electrical devices or appliances

Inactive ingredients

citric acid, potassium sorbate, purified ionized mineral water

Questions or comments

You can email us at info@hellolife.net or call us toll-free at 1.800.875.0850 Monday through Friday 9am-5pm ET

DESCRIPTION

- 30-day supply
- dropper included
- Synaptol is made without alcohol or sugar. No gluten added.

Mftd for: HelloLife, Inc.

4460 44th St. SE, Ste. C-600

Grand Rapids, MI 49512

FDA Pharmaceutical Establishment #1053442, #3009727070

www.synaptol.com

Principal Display Panel

NDC 49726-028-02

SYNAPTOL®
To temporarily relieve symptoms such as:

- hyperactivity

- impulsivity

- inattentiveness

- cannot concentrate when reading or studying

2 fl oz (59 mL)
Homeopathic (OTC) Medicine